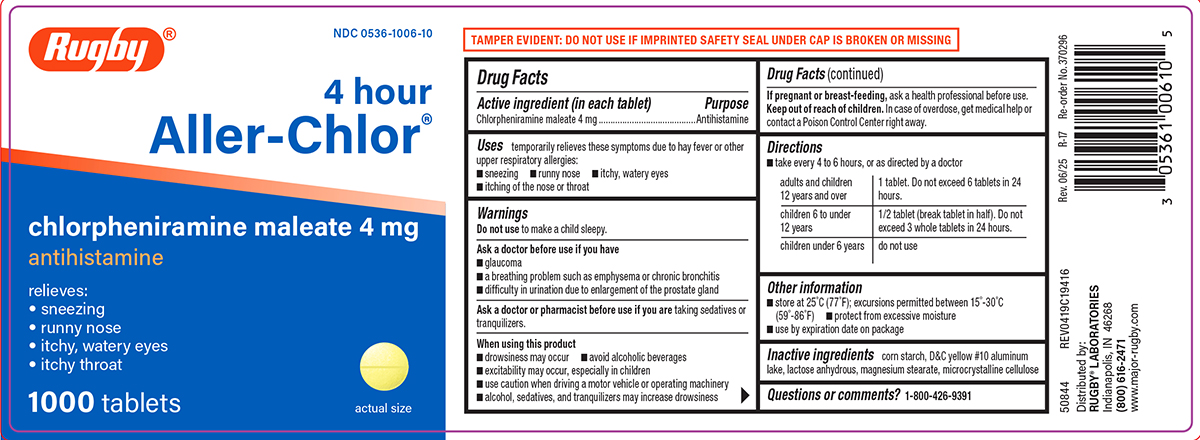 DRUG LABEL: Aller-chlor
NDC: 0536-1006 | Form: TABLET
Manufacturer: Rugby Laboratories
Category: otc | Type: HUMAN OTC DRUG LABEL
Date: 20250701

ACTIVE INGREDIENTS: CHLORPHENIRAMINE MALEATE 4 mg/1 1
INACTIVE INGREDIENTS: STARCH, CORN; D&C YELLOW NO. 10 ALUMINUM LAKE; ANHYDROUS LACTOSE; MAGNESIUM STEARATE; MICROCRYSTALLINE CELLULOSE

Rugby 44-194

Active ingredient (in each tablet)

Chlorpheniramine maleate 4 mg

Purpose

Antihistamine

Uses

temporarily relieves these symptoms due to hay fever or other upper respiratory allergies:

- runny nose
- itchy, watery eyes
- sneezing
- itching of the nose or throat

Warnings

Do not use

to make a child sleepy.

Ask a doctor before use if you have

- a breathing problem such as emphysema or chronic bronchitis
- difficulty in urination due to enlargement of the prostate gland
- glaucoma

Ask a doctor or pharmacist before use if you are

taking sedatives or tranquilizers.

When using this product

- drowsiness may occur
- avoid alcoholic beverages
- alcohol, sedatives, and tranquilizers may increase drowsiness
- use caution when driving a motor vehicle or operating machinery
- excitability may occur, especially in children

If pregnant or breast-feeding,

ask a health professional before use.

Keep out of reach of children.

In case of overdose, get medical help or contact a Poison Control Center right away.

Directions

- take every 4 to 6 hours, or as directed by a doctor

adults and children 12 years and over | 1 tablet. Do not exceed 6 tablets in 24 hours.
children 6 to under 12 years | 1/2 tablet (break tablet in half). Do not exceed 3 whole tablets in 24 hours.
children under 6 years | do not use

Other information

- store at 25ºC (77ºF); excursions permitted between 15º-30ºC (59º-86ºF)
- protect from excessive moisture
- use by expiration date on package

Inactive ingredients

corn starch, D&C yellow #10 aluminum lake, lactose anhydrous, magnesium stearate, microcrystalline cellulose

Questions or comments?

1-800-426-9391

Principal Display Panel

Rugby®

NDC 0536-1006-10

4 Hour

Aller-chlor®

Chlorpheniramine Maleate 4 mg
Antihistamine

relieves:
• sneezing
• runny nose
• itchy, watery eyes
• itchy throat

1000 Tablets

actual size

TAMPER EVIDENT: DO NOT USE IF IMPRINTED SAFETY SEAL UNDER CAP IS BROKEN OR MISSING

50844 REV0419C19416

Distributed by:
RUGBY® LABORATORIES
Indianapolis, IN 46268
(800) 616-2471
www.major-rugby.com

Rev. 06/25 R-17 Re-order No. 370296

Rugby 44-194